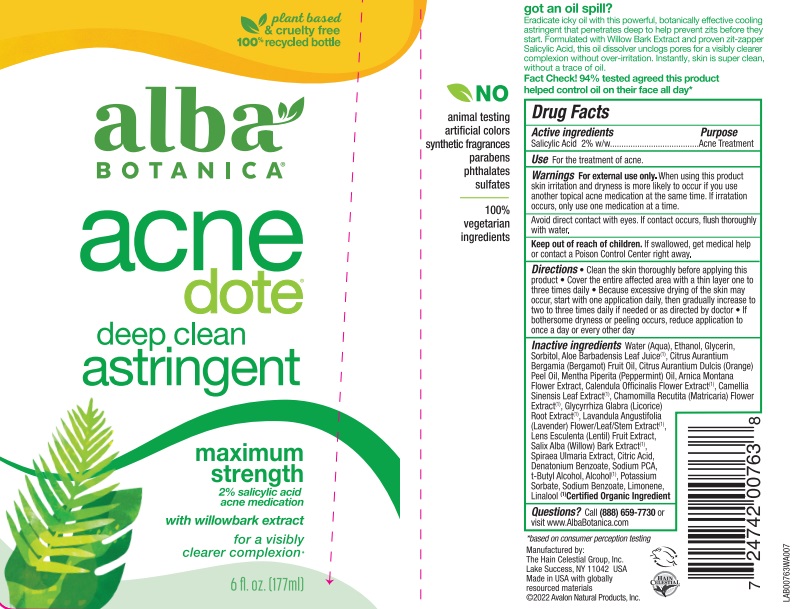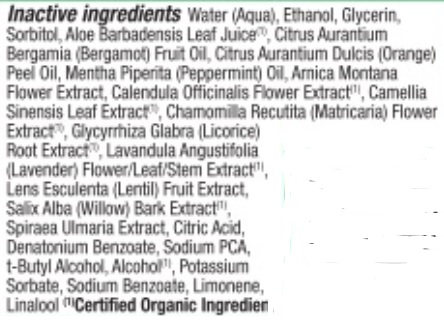 DRUG LABEL: Alba Natural Acnedote Astringent
NDC: 61995-2753 | Form: LOTION
Manufacturer: The Hain Celestial Group, Inc.
Category: otc | Type: HUMAN OTC DRUG LABEL
Date: 20240731

ACTIVE INGREDIENTS: SALICYLIC ACID 2 g/100 g
INACTIVE INGREDIENTS: ARNICA MONTANA FLOWER WATER; WATER; MYRICA ESCULENTA FRUIT; LINALOOL, (+)-; ALOE VERA LEAF; CALENDULA OFFICINALIS FLOWER; CAMELLIA SINENSIS WHOLE; SORBITOL; SODIUM BENZOATE; LIMONENE, (+)-; ALCOHOL 95%; ORANGE PEEL; PEPPERMINT OIL; ANHYDROUS CITRIC ACID; TERT-BUTYL ALCOHOL; GLYCERIN; FILIPENDULA ULMARIA WHOLE; MATRICARIA CHAMOMILLA; GLYCYRRHIZA GLABRA; LAVENDER OIL; WILLOW BARK; POTASSIUM SORBATE; DENATONIUM BENZOATE; CITRUS AURANTIUM FRUIT OIL

AL00763 Alba Natural Acnedote Astringent.
IL per label artwork.

ACTIVE INGREDIENTS

Salicylic Acid 2.0%

USE

- For the treatment of acne
- Apply with a cotton ball to freshly cleansed face morning an evening
- For the best results, follow with Alba Botanica Natural ACNEdote Invisible Treatment Gel.

WARNINGS

For external use only. Using other topical acne medications at the same time or immediately following the use of this product may increase dryness or irritation of the skin. If this occurs,only one drug should be used unless directed by a doctor.

Avoid direct contact with eyes. If contact occurs, flush thoroughly with water.

Keep out of reach of children. If swallowed, get medical help or contact a Poison Control Center right away.

QUESTIONS?

Call (888) 659-7730 or visit www.AlbaBotanica.com

The Hain Celestial Group, Inc.

ACTIVE INGREDIENT

Salicylic Acid 2.0% w/w

DOSAGE AND ADMINISTRATION

Lotion

Keep out of reach of children.

PURPOSE

Controls Acne